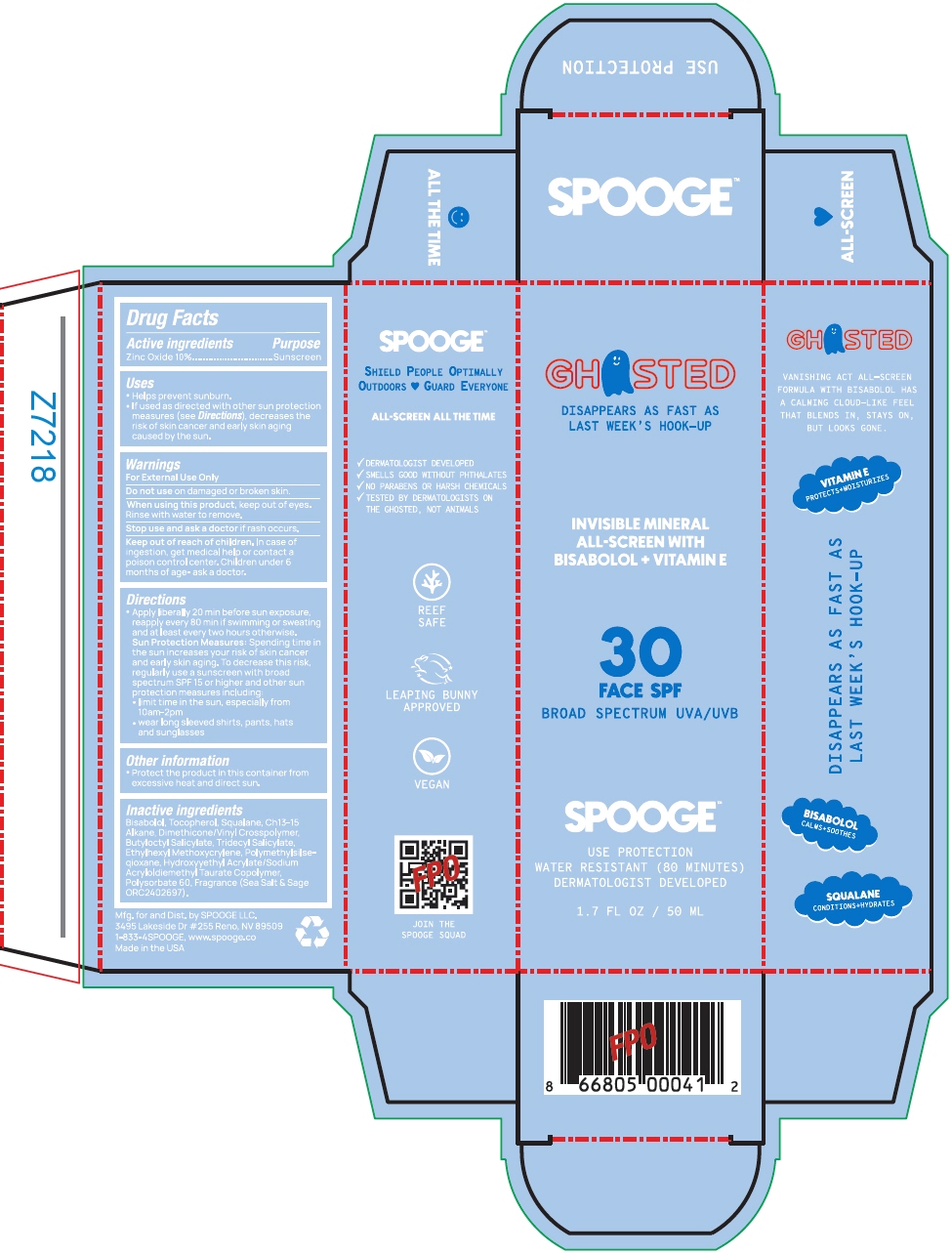 DRUG LABEL: GHOSTED
NDC: 85385-246 | Form: LOTION
Manufacturer: Spooge
Category: otc | Type: HUMAN OTC DRUG LABEL
Date: 20250626

ACTIVE INGREDIENTS: Zinc Oxide 100 mg/1 mL
INACTIVE INGREDIENTS: LEVOMENOL; Tocopherol; Squalane; Butyloctyl SalIcylate; Tridecyl SalIcylate; Ethylhexyl Methoxycrylene; Polysorbate 60; Sea Salt; Sage

GHOSTED

Drug Facts

Active ingredients

Zinc Oxide 10%

Purpose

Sunscreen

Uses

- Helps prevent sunburn.
- If used as directed with other sun protection measures (see Directions), decreases the risk of skin cancer and early skin aging caused by the sun.

Warnings

For External Use Only

Do not use on damaged or broken skin.

When using this product, keep out of eyes. Rinse with water to remove.

Stop use and ask a doctor if rash occurs.

Keep out of reach of children. In case of ingestion, get medical help or contact a poison control center. Children under 6 months of age- ask a doctor.

Directions

- Apply liberally 20 min before sun exposure, reapply every 80 min if swimming or sweating and at least every two hours otherwise.
  Sun Protection Measures: Spending time in the sun increases your risk of skin cancer and early skin aging. To decrease this risk, regularly use a sunscreen with broad spectrum SPF 15 or higher and other sun protection measures including:
  - limit time in the sun, especially from 10am-2pm
  - wear long sleeved shirts, pants, hats and sunglasses

Other information

- Protect the product in this container from excessive heat and direct sun.

Inactive ingredients

Bisabolol, Tocopherol, Squalane, Ch13-15 Alkane, Dimethicone/Vinyl Crosspolymer, Butyloctyl Salicylate, Tridecyl Salicylate, Ethylhexyl Methoxycrylene, Polymethylsilseqioxane, Hydroxyyethyl Acrylate/Sodium Acryloldiemethyl Taurate Copolymer, Polysorbate 60, Fragrance (Sea Salt & Sage ORC2402697).

Dist. by SPOOGE LLC.
3495 Lakeside Dr #255 Reno, NV 89509

PRINCIPAL DISPLAY PANEL - 50 ML Bottle Box

GHOSTED

DISAPPEARS AS FAST AS
LAST WEEK'S HOOK-UP

INVISIBLE MINERAL
ALL-SCREEN WITH
BISABOLOL + VITAMIN E

30
FACE SPF
BROAD SPECTRUM UVA/UVB

SPOOGE™

USE PROTECTION
WATER RESISTANT (80 MINUTES)
DERMATOLOGIST DEVELOPED

1.7 FL OZ / 50 ML